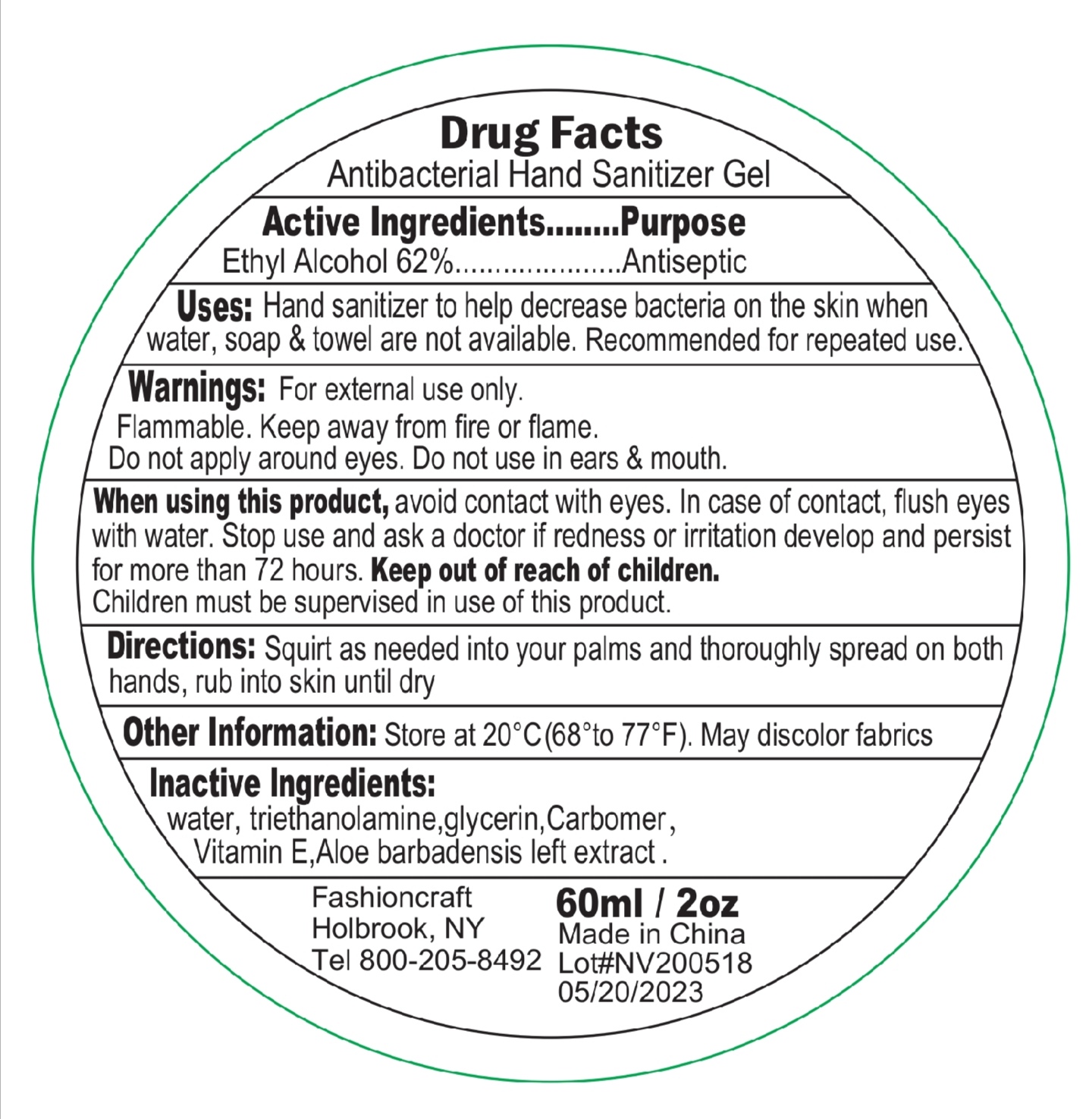 DRUG LABEL: Antibacterial Hand Sanitizer
NDC: 76114-011 | Form: GEL
Manufacturer: Zhejiang Aidi Cosmetics Co., Ltd
Category: otc | Type: HUMAN OTC DRUG LABEL
Date: 20200803

ACTIVE INGREDIENTS: ALCOHOL 62 mL/100 mL
INACTIVE INGREDIENTS: GLYCERIN; WATER; CARBOMER 940; TROLAMINE; ALOE VERA LEAF; .ALPHA.-TOCOPHEROL ACETATE

76114-011

Active Ingredient(s)

Ethyl Alcohol 62% v/v

Purpose

Antiseptic

Use

Hand sanitizer to help decrease bacteria on the skin

When water, soap, and towel are not available

Recommended for repeaded use

Warnings

For external use only.

Flammable. Keep away from fire or flame

Do not apply around eyes. Do not use in ears and mouth

When using this product avoid contact with eyes. In case of contact, flush eyes with water.

Stop use and ask a doctor if redness or irritation develops and persists for more than 72 hours

Keep out of reach of children. Children must be supervised in use of this product.

Directions

Squirt as needed into your palms and thoroughly spread on both hands, rub into skin until dry

Other information

Store at 20C (68-77F)

May discolor fabrics

Inactive ingredients

Water, triethanolamine, carbomer, fragrance, glycerin, tocopheryl acetate (Vitamin E), Aloe barbadensis leaf extract